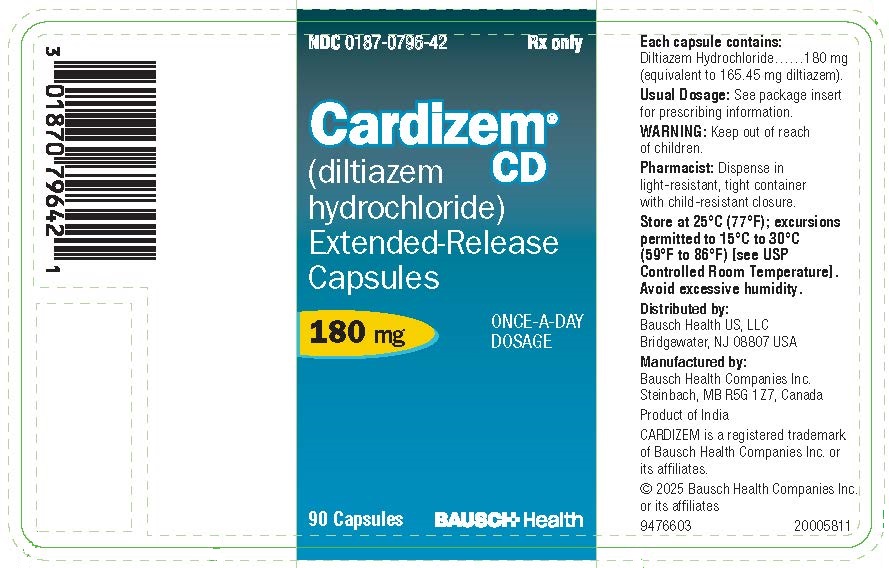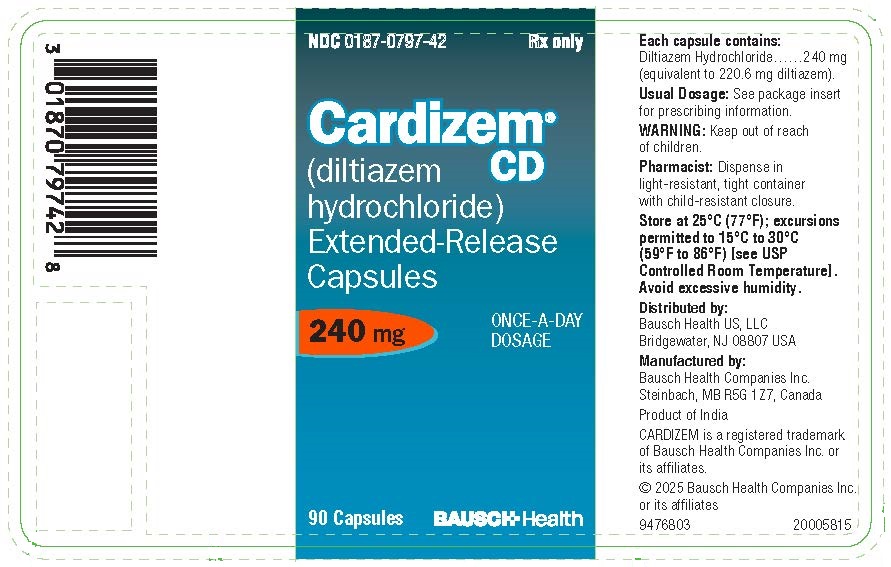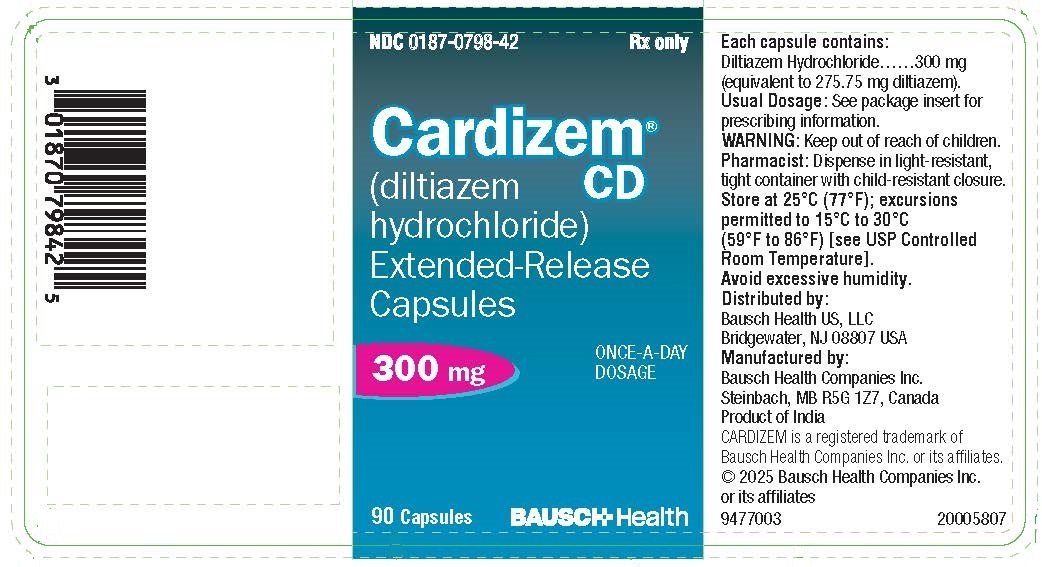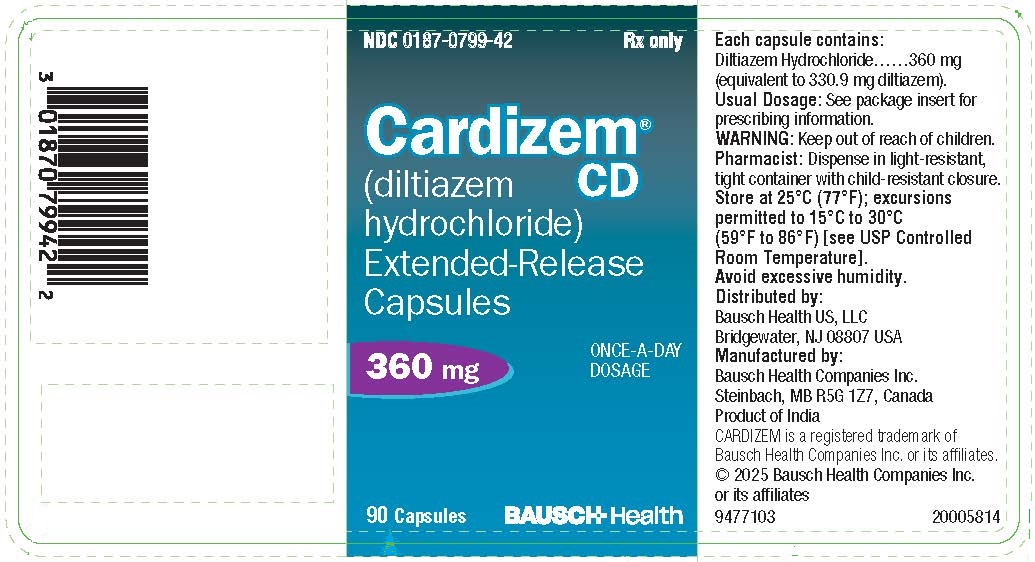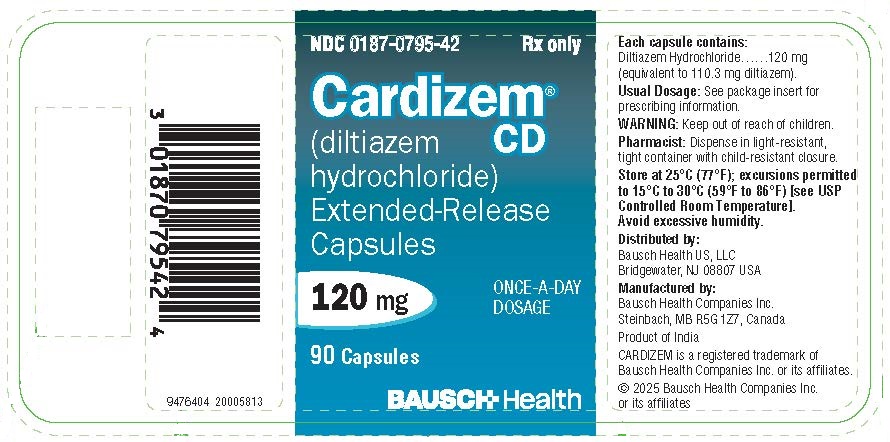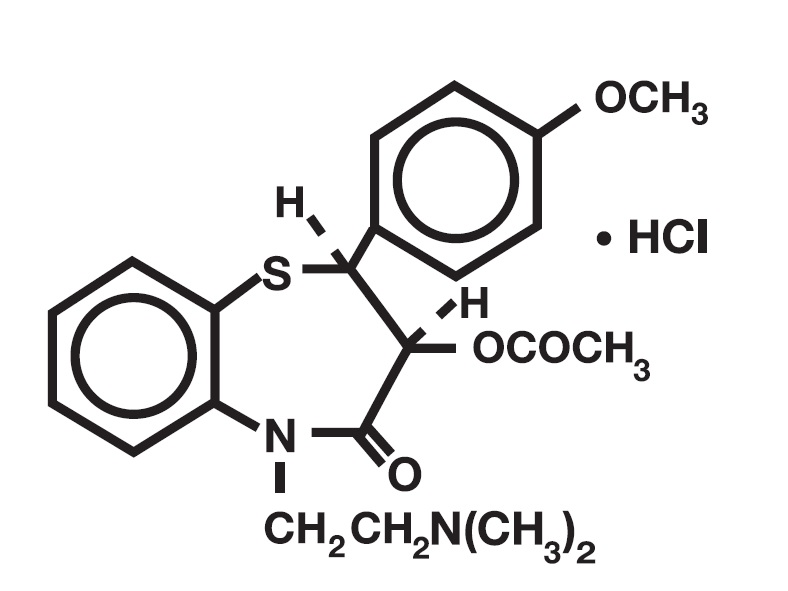 DRUG LABEL: Cardizem CD
NDC: 0187-0795 | Form: CAPSULE, COATED, EXTENDED RELEASE
Manufacturer: Bausch Health US LLC
Category: prescription | Type: HUMAN PRESCRIPTION DRUG LABEL
Date: 20251210

ACTIVE INGREDIENTS: DILTIAZEM HYDROCHLORIDE 120 mg/1 1
INACTIVE INGREDIENTS: FERROSOFERRIC OXIDE 300 mg/1 1; FD&C BLUE NO. 1; MAGNESIUM STEARATE; ETHYL ACRYLATE AND METHYL METHACRYLATE COPOLYMER (2:1; 750000 MW); POLYSORBATE 80; POVIDONE K30; SUCROSE STEARATE; TALC; TITANIUM DIOXIDE; GELATIN, UNSPECIFIED; HYPROMELLOSE, UNSPECIFIED; MICROCRYSTALLINE CELLULOSE

CARDIZEM® CD (diltiazem hydrochloride) Extended-Release Capsules

DESCRIPTION

CARDIZEM® CD (diltiazem hydrochloride) is a calcium ion cellular influx inhibitor (slow channel blocker or calcium antagonist). Chemically, diltiazem hydrochloride is 1,5-Benzothiazepin-4(5H)-one, 3-(acetyloxy)-5-[2-(dimethylamino) ethyl]-2, 3-dihydro-2-(4-methoxyphenyl)-, monohydrochloride, (+)-cis-. The chemical structure is:

Diltiazem hydrochloride is a white to off-white crystalline powder with a bitter taste. It is soluble in water, methanol, and chloroform. It has a molecular weight of 450.98. CARDIZEM CD is formulated as a once-a-day extended-release capsule containing 120 mg diltiazem hydrochloride (equivalent to 110.3 mg diltiazem), 180 mg diltiazem hydrochloride (equivalent to 165.45 mg diltiazem), 240 mg diltiazem hydrochloride (equivalent to 220.6 mg diltiazem), 300 mg diltiazem hydrochloride (equivalent to 275.75 mg diltiazem), or 360 mg diltiazem hydrochloride (equivalent to 330.9 mg diltiazem).

Capsules also contain: black iron oxide (300 mg), FD&C Blue #1, gelatin, hypromellose, magnesium stearate, microcrystalline cellulose, ethyl acrylate and methyl methacrylate copolymer, polysorbate, povidone, simethicone emulsion, sucrose stearate, talc, and titanium dioxide.

For oral administration.

CLINICAL PHARMACOLOGY

The therapeutic effects of diltiazem are believed to be related to its ability to inhibit the cellular influx of calcium ions during membrane depolarization of cardiac and vascular smooth muscle.

Mechanisms of Action

Hypertension: Diltiazem produces its antihypertensive effect primarily by relaxation of vascular smooth muscle and the resultant decrease in peripheral vascular resistance. The magnitude of blood pressure reduction is related to the degree of hypertension; thus hypertensive individuals experience an antihypertensive effect, whereas there is only a modest fall in blood pressure in normotensives.

Angina: Diltiazem has been shown to produce increases in exercise tolerance, probably due to its ability to reduce myocardial oxygen demand. This is accomplished via reductions in heart rate and systemic blood pressure at submaximal and maximal workloads. Diltiazem has been shown to be a potent dilator of coronary arteries, both epicardial and subendocardial. Spontaneous and ergonovine-induced coronary artery spasms are inhibited by diltiazem.

In animal models, diltiazem interferes with the slow inward (depolarizing) current in excitable tissue. It causes excitation-contraction uncoupling in various myocardial tissues without changes in the configuration of the action potential. Diltiazem produces relaxation of coronary vascular smooth muscle and dilation of both large and small coronary arteries at drug levels that cause little or no negative inotropic effect. The resultant increases in coronary blood flow (epicardial and subendocardial) occur in ischemic and nonischemic models and are accompanied by dose-dependent decreases in systemic blood pressure and decreases in peripheral resistance.

Hemodynamic and Electrophysiologic Effects

Like other calcium channel antagonists, diltiazem decreases sinoatrial and atrioventricular conduction in isolated tissues and has a negative inotropic effect in isolated preparations. In the intact animal, prolongation of the AH interval can be seen at higher doses.

In man, diltiazem prevents spontaneous and ergonovine-provoked coronary artery spasm. It causes a decrease in peripheral vascular resistance and a modest fall in blood pressure in normotensive individuals and, in exercise tolerance studies in patients with ischemic heart disease, reduces the heart rate-blood pressure product for any given workload. Studies, primarily in patients with good ventricular function, have not revealed evidence of a negative inotropic effect; cardiac output, ejection fraction, and left ventricular end diastolic pressure have not been affected. Such data have no predictive value with respect to effects in patients with poor ventricular function, and increased heart failure has been reported in patients with preexisting impairment of ventricular function. There are few data on the interaction of diltiazem and beta-blockers in patients with poor ventricular function. Resting heart rate is usually slightly reduced by diltiazem.

In hypertensive patients, CARDIZEM CD produces antihypertensive effects both in the supine and standing positions. In a double-blind, parallel, dose-response study utilizing doses ranging from 90 to 540 mg once daily, CARDIZEM CD lowered supine diastolic blood pressure in an apparent linear manner over the entire dose range studied. The changes in diastolic blood pressure, measured at trough, for placebo, 90 mg, 180 mg, 360 mg, and 540 mg were –2.9, –4.5, –6.1, –9.5, and –10.5 mm Hg, respectively. Postural hypotension is infrequently noted upon suddenly assuming an upright position. No reflex tachycardia is associated with the chronic antihypertensive effects. CARDIZEM CD decreases vascular resistance, increases cardiac output (by increasing stroke volume), and produces a slight decrease or no change in heart rate. During dynamic exercise, increases in diastolic pressure are inhibited, while maximum achievable systolic pressure is usually reduced. Chronic therapy with CARDIZEM CD produces no change or an increase in plasma catecholamines. No increased activity of the renin-angiotensin-aldosterone axis has been observed. CARDIZEM CD reduces the renal and peripheral effects of angiotensin II. Hypertensive animal models respond to diltiazem with reductions in blood pressure and increased urinary output and natriuresis without a change in urinary sodium/potassium ratio.

In a double-blind, parallel dose-response study of doses from 60 mg to 480 mg once daily, CARDIZEM CD increased time to termination of exercise in a linear manner over the entire dose range studied. The improvement in time to termination of exercise utilizing a Bruce exercise protocol, measured at trough, for placebo, 60 mg, 120 mg, 240 mg, 360 mg, and 480 mg was 29, 40, 56, 51, 69, and 68 seconds, respectively. As doses of CARDIZEM CD were increased, overall angina frequency was decreased. CARDIZEM CD, 180 mg once daily, or placebo was administered in a double-blind study to patients receiving concomitant treatment with long-acting nitrates and/or beta-blockers. A significant increase in time to termination of exercise and a significant decrease in overall angina frequency was observed. In this trial the overall frequency of adverse events in the CARDIZEM CD treatment group was the same as the placebo group.

Intravenous diltiazem in doses of 20 mg prolongs AH conduction time and AV node functional and effective refractory periods by approximately 20%. In a study involving single oral doses of diltiazem hydrochloride 300 mg in six normal volunteers, the average maximum PR prolongation was 14% with no instances of greater than first-degree AV block. Diltiazem-associated prolongation of the AH interval is not more pronounced in patients with first-degree heart block. In patients with sick sinus syndrome, diltiazem significantly prolongs sinus cycle length (up to 50% in some cases).

Chronic oral administration of diltiazem hydrochloride to patients in doses of up to 540 mg/day has resulted in small increases in PR interval and on occasion produces abnormal prolongation (see WARNINGS).

Pharmacokinetics and Metabolism

Diltiazem is well absorbed from the gastrointestinal tract and is subject to an extensive first-pass effect, giving an absolute bioavailability (compared to intravenous administration) of about 40%. Diltiazem undergoes extensive metabolism in which only 2% to 4% of the unchanged drug appears in the urine. Drugs which induce or inhibit hepatic microsomal enzymes may alter diltiazem disposition.

Total radioactivity measurement following short IV administration in healthy volunteers suggests the presence of other unidentified metabolites, which attain higher concentrations than those of diltiazem and are more slowly eliminated; half-life of total radioactivity is about 20 hours compared to 2 to 5 hours for diltiazem.

In vitro binding studies show diltiazem is 70% to 80% bound to plasma proteins. Competitive in vitro ligand binding studies have also shown diltiazem hydrochloride binding is not altered by therapeutic concentrations of digoxin, hydrochlorothiazide, phenylbutazone, propranolol, salicylic acid, or warfarin. The plasma elimination half-life following single or multiple drug administration is approximately 3.0 to 4.5 hours. Desacetyl diltiazem is also present in the plasma at levels of 10% to 20% of the parent drug and is 25% to 50% as potent as a coronary vasodilator as diltiazem. Minimum therapeutic plasma diltiazem concentrations appear to be in the range of 50 to 200 ng/mL. There is a departure from linearity when dose strengths are increased; the half-life is slightly increased with dose. A study that compared patients with normal hepatic function to patients with cirrhosis found an increase in half-life and a 69% increase in bioavailability in the hepatically impaired patients. A single study in nine patients with severely impaired renal function showed no difference in the pharmacokinetic profile of diltiazem compared to patients with normal renal function.

CARDIZEM CD Capsules: When compared to a regimen of CARDIZEM tablets at steady-state, more than 95% of drug is absorbed from the CARDIZEM CD formulation. A single 360 mg dose of the capsule results in detectable plasma levels within 2 hours and peak plasma levels between 10 and 14 hours; absorption occurs throughout the dosing interval. When CARDIZEM CD was coadministered with a high fat content breakfast, the extent of diltiazem absorption was not affected. Dose-dumping does not occur. The apparent elimination half-life after single or multiple dosing is 5 to 8 hours. A departure from linearity similar to that seen with CARDIZEM tablets and CARDIZEM SR capsules is observed. As the dose of CARDIZEM CD capsules is increased from a daily dose of 120 mg to 240 mg, there is an increase in the area under the curve (AUC) of 2.7 times. When the dose is increased from 240 mg to 360 mg, there is an increase in AUC of 1.6 times.

In an in vitro dissolution study, the release rate of diltiazem from CARDIZEM CD increased significantly as the alcohol percentage in the dissolution medium increased. The effect of alcohol on the release rate may lead to a change in the pharmacokinetics of diltiazem, such as a more rapid absorption and/or an increase in the systemic exposure of diltiazem (see PRECAUTIONS, Drug Interactions).

INDICATIONS AND USAGE

CARDIZEM CD is indicated for the treatment of hypertension. It may be used alone or in combination with other antihypertensive medications.

CARDIZEM CD is indicated for the management of chronic stable angina and angina due to coronary artery spasm.

CONTRAINDICATIONS

CARDIZEM CD is contraindicated in (1) patients with sick sinus syndrome except in the presence of a functioning ventricular pacemaker, (2) patients with second- or third-degree AV block except in the presence of a functioning ventricular pacemaker, (3) patients with hypotension (less than 90 mm Hg systolic), (4) patients who have demonstrated hypersensitivity to the drug, and (5) patients with acute myocardial infarction and pulmonary congestion documented by x-ray on admission.

WARNINGS

Cardiac Conduction: Diltiazem hydrochloride prolongs AV node refractory periods without significantly prolonging sinus node recovery time, except in patients with sick sinus syndrome. This effect may rarely result in abnormally slow heart rates (particularly in patients with sick sinus syndrome) or second- or third-degree AV block (13 of 3290 patients or 0.40%). Concomitant use of diltiazem with beta-blockers or digitalis may result in additive effects on cardiac conduction. A patient with Prinzmetal’s angina developed periods of asystole (2 to 5 seconds) after a single dose of 60 mg of diltiazem (see ADVERSE REACTIONS).

Congestive Heart Failure: Although diltiazem has a negative inotropic effect in isolated animal tissue preparations, hemodynamic studies in humans with normal ventricular function have not shown a reduction in cardiac index nor consistent negative effects on contractility (dP/dt). An acute study of oral diltiazem in patients with impaired ventricular function (ejection fraction 24% ± 6%) showed improvement in indices of ventricular function without significant decrease in contractile function (dP/dt). Worsening of congestive heart failure has been reported in patients with preexisting impairment of ventricular function. Experience with the use of diltiazem hydrochloride in combination with beta-blockers in patients with impaired ventricular function is limited. Caution should be exercised when using this combination.

Hypotension: Decreases in blood pressure associated with diltiazem hydrochloride therapy may occasionally result in symptomatic hypotension.

Acute Hepatic Injury: Mild elevations of transaminases with and without concomitant elevation in alkaline phosphatase and bilirubin have been observed in clinical studies. Such elevations were usually transient and frequently resolved even with continued diltiazem treatment. In rare instances, significant elevations in enzymes such as alkaline phosphatase, LDH, SGOT, SGPT, and other phenomena consistent with acute hepatic injury have been noted. These reactions tended to occur early after therapy initiation (1 to 8 weeks) and have been reversible upon discontinuation of drug therapy. The relationship to diltiazem hydrochloride is uncertain in some cases, but probable in some (see PRECAUTIONS).

PRECAUTIONS

General

Diltiazem hydrochloride is extensively metabolized by the liver and excreted by the kidneys and in bile. Laboratory parameters of renal and hepatic function should be monitored at regular intervals. In subacute and chronic dog and rat studies designed to produce toxicity, high doses of diltiazem were associated with hepatic damage. In special subacute hepatic studies, oral doses of 125 mg/kg and higher in rats were associated with histological changes in the liver which were reversible when the drug was discontinued. In dogs, doses of 20 mg/kg were also associated with hepatic changes; however, these changes were reversible with continued dosing.

Dermatological events (see ADVERSE REACTIONS) may be transient and may disappear despite continued use of diltiazem hydrochloride. However, skin eruptions progressing to erythema multiforme and/or exfoliative dermatitis have also been infrequently reported. Should a dermatologic reaction persist, the drug should be discontinued.

Drug Interactions

Because of the potential for additive effects, slow titration is warranted in patients receiving diltiazem hydrochloride concomitantly with other agents known to affect cardiac contractility and/or conduction (see WARNINGS). Pharmacologic studies indicate that there may be additive effects in prolonging AV conduction when using beta-blockers or digitalis concomitantly with CARDIZEM CD (see WARNINGS).

Diltiazem is both a substrate and an inhibitor of the Pg-p and cytochrome P450 3A4 enzyme system which may affect exposure to diltiazem and concomitant drugs metabolized by those pathways. Patients with renal and/or hepatic impairment may be particularly at risk of exposure changes.

Anesthetics: The depression of cardiac contractility, conductivity, and automaticity as well as the vascular dilation associated with anesthetics may be potentiated by calcium channel blockers. When used concomitantly, titrate anesthetics and calcium blockers slowly.

Benzodiazepines: Studies showed that diltiazem increased the AUC of midazolam and triazolam by 3- to 4-fold and the Cmax by 2-fold, compared to placebo. The elimination half-life of midazolam and triazolam also increased (1.5- to 2.5-fold) during coadministration with diltiazem. These pharmacokinetic effects seen during diltiazem coadministration can result in increased clinical effects (e.g., prolonged sedation) of both midazolam and triazolam.

Beta-blockers: Controlled and uncontrolled domestic studies suggest that concomitant use of diltiazem hydrochloride and beta-blockers is usually well tolerated, but available data are not sufficient to predict the effects of concomitant treatment in patients with left ventricular dysfunction or cardiac conduction abnormalities.

Administration of diltiazem hydrochloride concomitantly with propranolol in five normal volunteers resulted in increased propranolol levels in all subjects and bioavailability of propranolol was increased approximately 50%. In vitro, propranolol appears to be displaced from its binding sites by diltiazem. If combination therapy is initiated or withdrawn in conjunction with propranolol, an adjustment in the propranolol dose may be warranted (see WARNINGS).

Buspirone: In nine healthy subjects, diltiazem significantly increased the mean buspirone AUC 5.5-fold and Cmax 4.1-fold compared to placebo. The T1/2 and Tmax of buspirone were not significantly affected by diltiazem. Enhanced effects and increased toxicity of buspirone may be possible during concomitant administration with diltiazem. Subsequent dose adjustments may be necessary during coadministration, and should be based on clinical assessment.

Carbamazepine: Concomitant administration of diltiazem with carbamazepine has been reported to result in elevated serum levels of carbamazepine (40% to 72% increase), resulting in toxicity in some cases.

Cimetidine: A study in six healthy volunteers has shown a significant increase in peak diltiazem plasma levels (58%) and AUC (53%) after a 1-week course of cimetidine at 1200 mg per day and a single dose of diltiazem 60 mg. Ranitidine produced smaller, nonsignificant increases. The effect may be mediated by cimetidine’s known inhibition of hepatic cytochrome P450, the enzyme system responsible for the first-pass metabolism of diltiazem. Patients currently receiving diltiazem therapy should be carefully monitored for a change in pharmacological effect when initiating and discontinuing therapy with cimetidine.

An adjustment in the diltiazem dose may be warranted.

Clonidine: Sinus bradycardia resulting in hospitalization and pacemaker insertion has been reported in association with the use of clonidine concurrently with diltiazem. Monitor heart rate in patients receiving concomitant diltiazem and clonidine.

Cyclosporine: A pharmacokinetic interaction between diltiazem and cyclosporine has been observed during studies involving renal and cardiac transplant patients. In renal and cardiac transplant recipients, a reduction of cyclosporine dose ranging from 15% to 48% was necessary to maintain cyclosporine trough concentrations similar to those seen prior to the addition of diltiazem. If these agents are to be administered concurrently, cyclosporine concentrations should be monitored, especially when diltiazem therapy is initiated, adjusted, or discontinued. The effect of cyclosporine on diltiazem plasma concentrations has not been evaluated.

Digitalis: Administration of diltiazem hydrochloride with digoxin in 24 healthy male subjects increased plasma digoxin concentrations approximately 20%. Another investigator found no increase in digoxin levels in 12 patients with coronary artery disease. Monitor digoxin levels when initiating, adjusting, and discontinuing diltiazem hydrochloride therapy to avoid possible over- or under-digitalization (see WARNINGS).

Ivabradine: Concurrent use of diltiazem increases exposure to ivabradine and may exacerbate bradycardia and conduction disturbances. Avoid concomitant use of ivabradine and diltiazem.

Quinidine: Diltiazem significantly increases the AUC(0-∞) of quinidine by 51%, T1/2 by 36%, and decreases its CLoral by 33%. Monitor for quinidine adverse effects and adjust the dose accordingly.

Rifampin: Coadministration of rifampin with diltiazem lowered the diltiazem plasma concentrations to undetectable levels. Avoid coadministration of diltiazem with rifampin or any known CYP3A4 inducer.

Statins: Diltiazem is an inhibitor of CYP3A4 and has been shown to increase significantly the AUC of some statins. The risk of myopathy and rhabdomyolysis with statins metabolized by CYP3A4 may be increased with concomitant use of diltiazem. When possible, use a non-CYP3A4-metabolized statin together with diltiazem; otherwise, monitor for signs and symptoms of any statin-related adverse events, and adjust the doses accordingly.

In a healthy volunteer crossover study (N=10), coadministration of a single 20 mg dose of simvastatin at the end of a 14-day regimen with 120 mg BID diltiazem SR resulted in a 5-fold increase in mean simvastatin AUC versus simvastatin alone. Subjects with increased average steady-state exposures of diltiazem showed a greater fold increase in simvastatin exposure. Computer-based simulations showed that at a daily dose of 480 mg of diltiazem, an 8- to 9-fold mean increase in simvastatin AUC can be expected. If coadministration of simvastatin with diltiazem is required, limit the daily doses of simvastatin to 10 mg and diltiazem to 240 mg.

In a ten-subject randomized, open-label, 4-way crossover study, coadministration of diltiazem (120 mg BID diltiazem SR for 2 weeks) with a single 20 mg dose of lovastatin resulted in 3- to 4-fold increase in mean lovastatin AUC and Cmax versus lovastatin alone. In the same study, there was no significant change in 20 mg single dose pravastatin AUC and Cmax during diltiazem coadministration. Diltiazem plasma levels were not significantly affected by lovastatin or pravastatin.

Alcohol: Alcohol increases the rate at which CARDIZEM CD releases diltiazem in vitro. This effect may lead to more rapid absorption and an increase in the systemic exposure of diltiazem, and associated dose-related adverse reactions. Avoid consumption of alcohol with CARDIZEM CD (see CLINICAL PHARMACOLOGY).

Carcinogenesis, Mutagenesis, Impairment of Fertility

A 24-month study in rats at oral dosage levels of up to 100 mg/kg/day and a 21-month study in mice at oral dosage levels of up to 30 mg/kg/day showed no evidence of carcinogenicity. There was also no mutagenic response in vitro or in vivo in mammalian cell assays or in vitro in bacteria. No evidence of impaired fertility was observed in a study performed in male and female rats at oral dosages of up to 100 mg/kg/day.

Pregnancy

Reproduction studies have been conducted in mice, rats, and rabbits. Administration of doses ranging from five to ten times greater (on a mg/kg basis) than the daily recommended therapeutic dose has resulted in embryo and fetal lethality. These doses, in some studies, have been reported to cause skeletal abnormalities. In the perinatal/postnatal studies, there was an increased incidence of stillbirths at doses of 20 times the human dose or greater.

There are no well-controlled studies in pregnant women; therefore, use diltiazem hydrochloride in pregnant women only if the potential benefit justifies the potential risk to the fetus.

Nursing Mothers

Diltiazem is excreted in human milk. One report suggests that concentrations in breast milk may approximate serum levels. If use of CARDIZEM CD is deemed essential, an alternative method of infant feeding should be instituted.

Pediatric Use

Safety and effectiveness in pediatric patients have not been established.

Geriatric Use

Clinical studies of diltiazem did not include sufficient numbers of subjects aged 65 and over to determine whether they respond differently from younger subjects. Other reported clinical experience has not identified differences in responses between the elderly and younger patients. In general, dose selection for an elderly patient should be cautious, usually starting at the low end of the dosing range, reflecting the greater frequency of decreased hepatic, renal, or cardiac function, and of concomitant disease or other drug therapy.

ADVERSE REACTIONS

Serious adverse reactions have been rare in studies carried out to date, but it should be recognized that patients with impaired ventricular function and cardiac conduction abnormalities have usually been excluded from these studies.

The following table presents the most common adverse reactions reported in placebo-controlled angina and hypertension trials in patients receiving CARDIZEM CD up to 360 mg with rates in placebo patients shown for comparison.

CARDIZEM CD Capsule Placebo-Controlled Angina and Hypertension Trials Combined
Adverse Reactions | CARDIZEM CD (n=607) | Placebo (n=301)
Headache | 5.4% | 5.0%
Dizziness | 3.0% | 3.0%
Bradycardia | 3.3% | 1.3%
AV Block First Degree | 3.3% | 0.0%
Edema | 2.6% | 1.3%
Asthenia | 1.8% | 1.7%

In addition, the following events were reported infrequently (less than 1%) in angina or hypertension trials:

Cardiovascular: Congestive heart failure, palpitations, syncope, ventricular extrasystoles.

Nervous System: Abnormal dreams, amnesia, depression, gait abnormality, hallucinations, insomnia, nervousness, paresthesia, personality change, somnolence, tinnitus, tremor.

Gastrointestinal: Anorexia, constipation, diarrhea, dry mouth, dysgeusia, dyspepsia, mild elevations of SGOT, SGPT, LDH, and alkaline phosphatase (see WARNINGS, Acute Hepatic Injury), thirst, vomiting, weight increase.

Dermatological: Petechiae, photosensitivity, pruritus, urticaria.

Other: Amblyopia, CPK increase, dyspnea, epistaxis, eye irritation, hyperglycemia, hyperuricemia, impotence, muscle cramps, nasal congestion, nocturia, osteoarticular pain, polyuria, sexual difficulties.

The following postmarketing events have been reported infrequently in patients receiving diltiazem hydrochloride: acute generalized exanthematous pustulosis, allergic reactions, alopecia, angioedema (including facial or periorbital edema), asystole, erythema multiforme (including Stevens-Johnson syndrome, toxic epidermal necrolysis), exfoliative dermatitis, extrapyramidal symptoms, gingival hyperplasia, hemolytic anemia, increased bleeding time, leukopenia, photosensitivity (including lichenoid keratosis and hyperpigmentation at sun-exposed skin areas), purpura, retinopathy, myopathy, and thrombocytopenia. In addition, events such as myocardial infarction have been observed which are not readily distinguishable from the natural history of the disease in these patients. A number of well-documented cases of generalized rash, some characterized as leukocytoclastic vasculitis, have been reported. However, a definitive cause and effect relationship between these events and diltiazem hydrochloride therapy is yet to be established.

To report SUSPECTED ADVERSE REACTIONS, contact Bausch Health US, LLC at 1-800-321-4576 or FDA at 1-800-FDA-1088 or www.fda.gov/medwatch.

OVERDOSAGE

The oral LD50s in mice and rats range from 415 to 740 mg/kg and from 560 to 810 mg/kg, respectively. The intravenous LD50s in these species were 60 and 38 mg/kg, respectively. The oral LD50 in dogs is considered to be in excess of 50 mg/kg, while lethality was seen in monkeys at 360 mg/kg.

The toxic dose in man is not known. Because of its extensive metabolism, blood levels after a standard dose of diltiazem can vary over tenfold, limiting the usefulness of blood levels in overdose cases.

There have been reports of diltiazem overdose in amounts ranging from <1 g to 18 g. Of cases with known outcome, most patients recovered and in cases with a fatal outcome, the majority involved multiple drug ingestion.

Events observed following diltiazem overdose included bradycardia, hypotension, heart block, and cardiac failure. Most reports of overdose described some supportive medical measure and/or drug treatment. Bradycardia frequently responded favorably to atropine, as did heart block, although cardiac pacing was also frequently utilized to treat heart block. Fluids and vasopressors were used to maintain blood pressure and in cases of cardiac failure, inotropic agents were administered. In addition, some patients received treatment with ventilatory support, gastric lavage, activated charcoal, and/or intravenous calcium.

In the event of overdose or exaggerated response, appropriate supportive measures should be employed in addition to gastrointestinal decontamination. Diltiazem does not appear to be removed by peritoneal or hemodialysis. Limited data suggest that plasmapheresis or charcoal hemoperfusion may hasten diltiazem elimination following overdose. Based on the known pharmacological effects of diltiazem and/or reported clinical experiences, the following measures may be considered:

Bradycardia: Administer atropine (0.60 to 1.0 mg). If there is no response to vagal blockade, administer isoproterenol cautiously.

High-degree AV Block: Treat as for bradycardia above. Fixed high-degree AV block should be treated with cardiac pacing.

Cardiac Failure: Administer inotropic agents (isoproterenol, dopamine, or dobutamine) and diuretics.

Hypotension: Vasopressors (e.g., dopamine or norepinephrine).

Actual treatment and dosage should depend on the severity of the clinical situation and the judgment and experience of the treating physician.

DOSAGE AND ADMINISTRATION

Patients controlled on diltiazem alone or in combination with other medications may be switched to CARDIZEM CD capsules at the nearest equivalent total daily dose. Higher doses of CARDIZEM CD may be needed in some patients. Monitor patients closely. Subsequent titration to higher or lower doses may be necessary. There is limited general clinical experience with doses above 360 mg, but doses to 540 mg have been studied in clinical trials. The incidence of side effects increases as the dose increases with first-degree AV block, dizziness, and sinus bradycardia bearing the strongest relationship to dose.

Hypertension: Adjust dosage to individual patient needs. When used as monotherapy, reasonable starting doses are 180 to 240 mg once daily, although some patients may respond to lower doses. Maximum antihypertensive effect is usually observed by 14 days of chronic therapy; therefore, schedule dosage adjustments accordingly. The usual dosage range studied in clinical trials was 240 to 360 mg once daily. Individual patients may respond to higher doses of up to 480 mg once daily.

Angina: Dosages for the treatment of angina should be adjusted to each patient’s needs, starting with a dose of 120 or 180 mg once daily. Individual patients may respond to higher doses of up to 480 mg once daily. When necessary, titration may be carried out over a 7- to 14-day period.

Concomitant Use with Other Cardiovascular Agents:

Sublingual NTG: May be taken as required to abort acute anginal attacks during diltiazem hydrochloride therapy.

Prophylactic Nitrate Therapy: Diltiazem hydrochloride may be safely coadministered with short- and long-acting nitrates.

Beta-blockers: (see WARNINGS and PRECAUTIONS.)

Antihypertensives: Diltiazem hydrochloride has an additive antihypertensive effect when used with other antihypertensive agents. Therefore, the dosage of diltiazem hydrochloride or the concomitant antihypertensives may need to be adjusted when adding one to the other.

HOW SUPPLIED

CARDIZEM® CD (diltiazem hydrochloride) Extended-Release Capsules
Strength | Quantity | NDC Number | Description
120 mg | 30 count 90 count | 0187-0795-30 0187-0795-42 | Light turquoise blue/light turquoise blue capsule imprinted with “cardizem CD 120 mg” on body.
180 mg | 30 count 90 count | 0187-0796-30 0187-0796-42 | Light blue/light turquoise blue capsule imprinted with “cardizem CD 180 mg” on body.
240 mg | 30 count 90 count | 0187-0797-30 0187-0797-42 | Light blue/light blue capsule imprinted with “cardizem CD 240 mg” on body.
300 mg | 30 count 90 count | 0187-0798-30 0187-0798-42 | Light blue/light gray capsule imprinted with “cardizem CD 300 mg” on body.
360 mg | 90 count | 0187-0799-42 | Light blue/white capsule imprinted with “cardizem CD 360 mg” on body.

Storage Conditions: Store at 25°C (77°F); excursions permitted to 15° to 30°C (59° to 86°F) [see USP Controlled Room Temperature]. Avoid excessive humidity.

Distributed by:
Bausch Health US, LLC
Bridgewater, NJ 08807 USA

Manufactured by:
Bausch Health Companies Inc.
Steinbach, MB R5G 1Z7, Canada

CARDIZEM is a registered trademark of Bausch Health Companies Inc. or its affiliates.
© 2025 Bausch Health Companies Inc. or its affiliates

Rev. 04/2025

9474004 20005830

Package/Label Display Panel -120 mg

NDC0187-0795-42

Rx only

CARDIZEM® CD

(diltiazem hydrochloride)

Extended-Release Capsules
ONCE-A-DAY
DOSAGE

120 mg

90 Capsules

BAUSCH HEALTH

Package/Label Display Panel – 180 mg

NDC0187-0796-42

Rx only

CARDIZEM® CD

(diltiazem hydrochloride)

Extended-Release Capsules
ONCE-A-DAY
DOSAGE

180 mg

90 Capsules

BAUSCH HEALTH

Package/Label Display Panel – 240 mg

NDC0187-0797-42

Rx only

CARDIZEM® CD

(diltiazem hydrochloride)

Extended-Release Capsules
ONCE-A-DAY
DOSAGE

240 mg

90 Capsules

BAUSCH HEALTH

Package/Label Display Panel – 300 mg

NDC0187-0798-42

Rx only

CARDIZEM® CD

(diltiazem hydrochloride)

Extended-Release Capsules
ONCE-A-DAY
DOSAGE

300 mg

90 Capsules

BAUSCH HEALTH

Package/Label Display Panel – 360 mg

NDC0187-0799-42

Rx only

CARDIZEM® CD

(diltiazem hydrochloride)

Extended-Release Capsules
ONCE-A-DAY DOSAGE

360 mg

90 Capsules

BAUSCH HEALTH